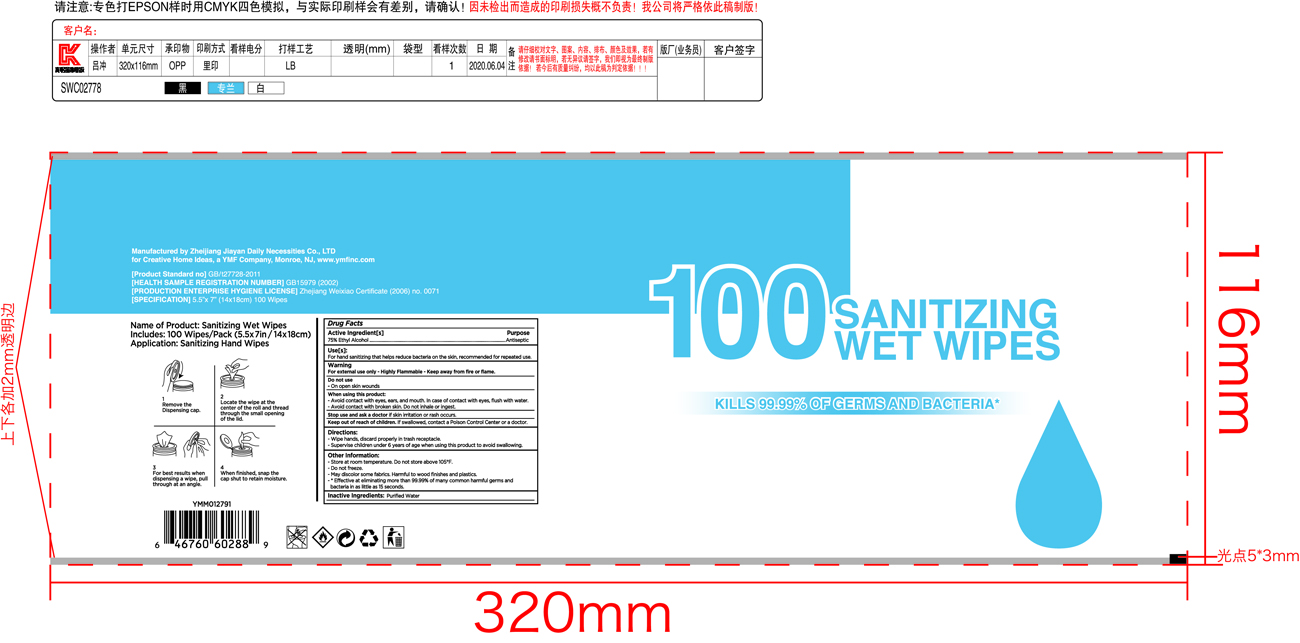 DRUG LABEL: sanitizing wipes
NDC: 78198-003 | Form: CLOTH
Manufacturer: Y M F Carpets, Inc.
Category: otc | Type: HUMAN OTC DRUG LABEL
Date: 20200625

ACTIVE INGREDIENTS: ALCOHOL 0.75 mL/1 g
INACTIVE INGREDIENTS: WATER

sanitizing wipes

ACTIVE INGREDIENT

Alcohol 75%. Purpose: Antiseptic

PURPOSE

Antiseptic

Use(s)

For hand sanitizing that helps reduce bacteria on the skin.

recommended for repeated use.

Warning

For external use only

Highly flammable

Keep away from fire or flame

Do not use

on open skin wounds

When using this product

Avoid contact with eyes, ears, and mouth. In case of contact with eyes, flush with water.

Avoid contact with broken skin. Do not inhale or ingest

Stop use and ask a doctor

if skin irritation or rash occurs.

KEEP OUT OF REACH OF CHILDREN

Keep our of reach of children. If swallowed, contact a Poison Control Center or a doctor.

Directions

- Wipe hands, discard properly in trash receptacle.

- Supervise children under 6 years of age when using this product to avoid swallowing.

Other information

- Store at room temperature. Do not store above 105F.

- Do not freeze.

- May discolor some fabrics.

- Harmful to wood finishes and plastics.

- * Effective at eliminating more than 99.99% of many common harmful germs and bacteria in as little as 15 seconds.

Inactive Ingredients

Purified Water

Package Label - Principal Display Panel

100 PCS NDC: 78198-003-01